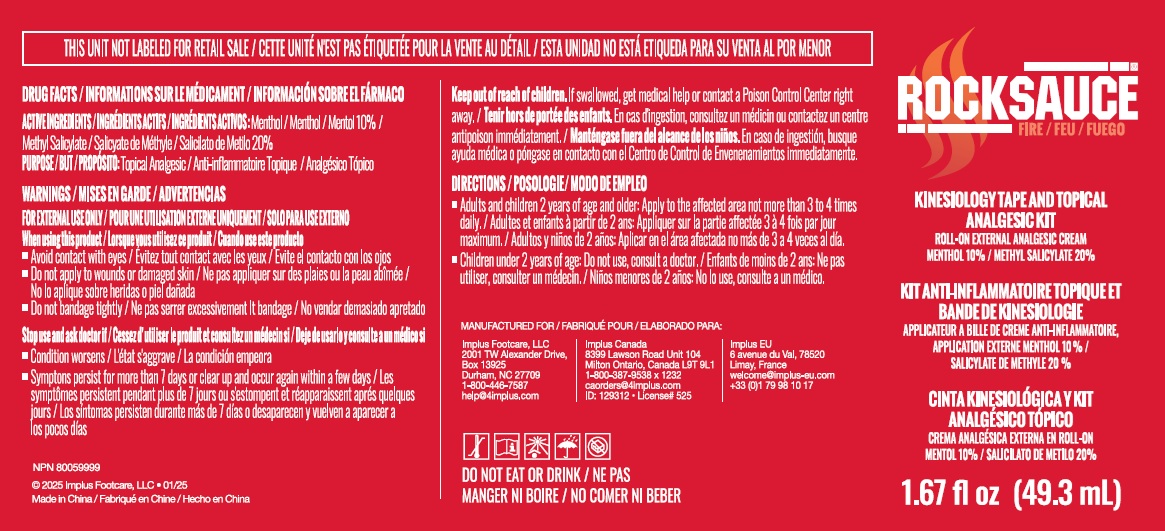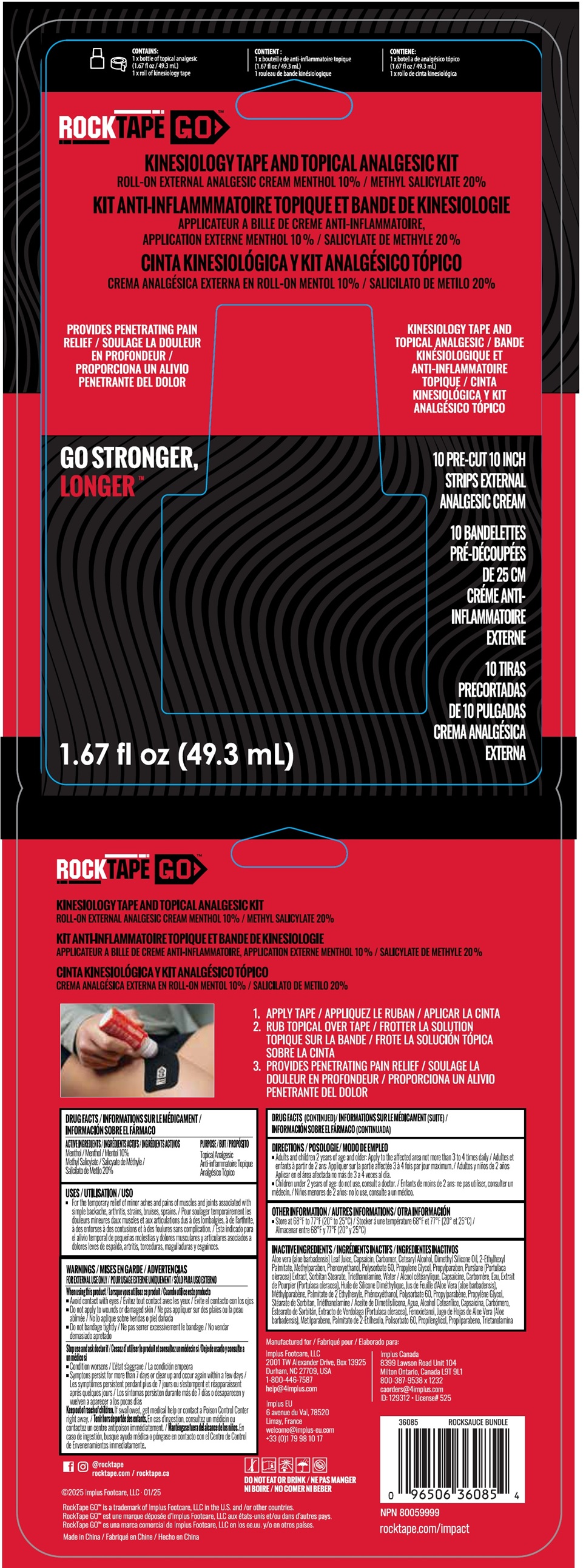 DRUG LABEL: ROCKTAPE GO Kinesiology Tape and Analgesic
NDC: 81683-001 | Form: KIT | Route: TOPICAL
Manufacturer: Implus Footcare, LLC
Category: otc | Type: HUMAN OTC DRUG LABEL
Date: 20260129

ACTIVE INGREDIENTS: MENTHOL 100 mg/1 mL; METHYL SALICYLATE 200 mg/1 mL
INACTIVE INGREDIENTS: ALOE VERA LEAF; CAPSAICIN; CARBOMER HOMOPOLYMER, UNSPECIFIED TYPE; CETOSTEARYL ALCOHOL; DIMETHICONE, UNSPECIFIED; ETHYLHEXYL PALMITATE; METHYLPARABEN; PHENOXYETHANOL; POLYSORBATE 60; PROPYLENE GLYCOL; PROPYLPARABEN; SORBITAN MONOSTEARATE; TRIETHANOLAMINE; WATER; PURSLANE

ROCKTAPE GO Kinesiology Tape and Topical Analgesic

ACTIVE INGREDIENTS

Menthol 10%
Methyl Salicylate 20%

PURPOSE

Topical Analgesic
Anti-inflammatoire Topique

USES

- For the temporary relief of minor aches and pains of muscles and joints associated with simple backache, arthritis, strains, bruises, sprains.

WARNINGS

FOR EXTERNAL USE ONLY

When using this product

- Avoid contact with eyes
- Do not apply to wounds or damaged skin
- Do not bandage tightly

Stop use and ask doctor if

- Condition worsens
- Symptoms persist for more than 7 days or clear up and occur again within a few days

Keep out of reach of children.

If swallowed, get medical help or contact a Poison Control Center right away.

DIRECTIONS

- Adults and children 2 years of age and older: Apply to the affected area not more than 3 to 4 times daily
- Children under 2 years of age: do not use, consult a doctor.

OTHER INFORMATION

- Store at 68°F to 77°F (20° to 25°C)

INACTIVE INGREDIENTS

Aloe vera [aloe barbadensis] Leaf Juice, Capsaicin, Carbomer, Cetearyl Alcohol, Dimethyl Silicone Oil, 2-Ethylhexyl Palmitate, Methylparaben, Phenoxyethanol, Polysorbate 60, Propylene Glycol, Propylparaben, Purslane (Portulaca oleracea) Extract, Sorbitan Stearate, Triethanolamine, Water